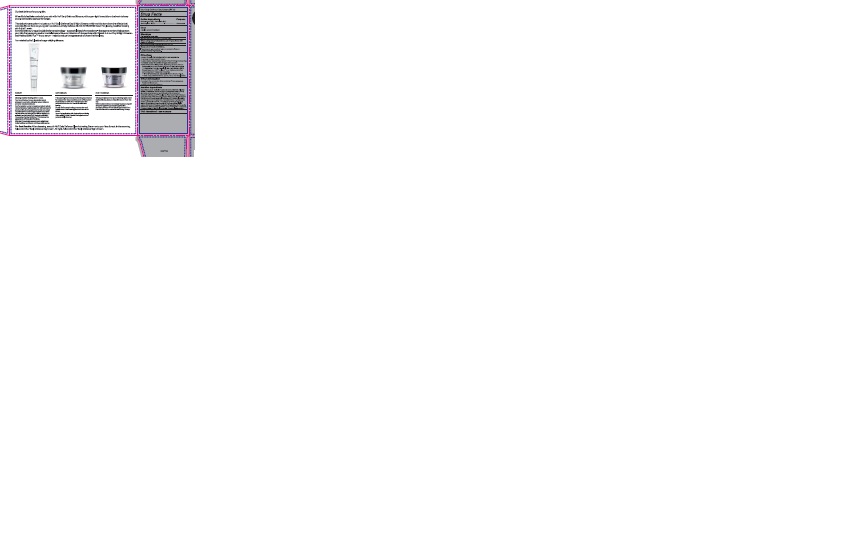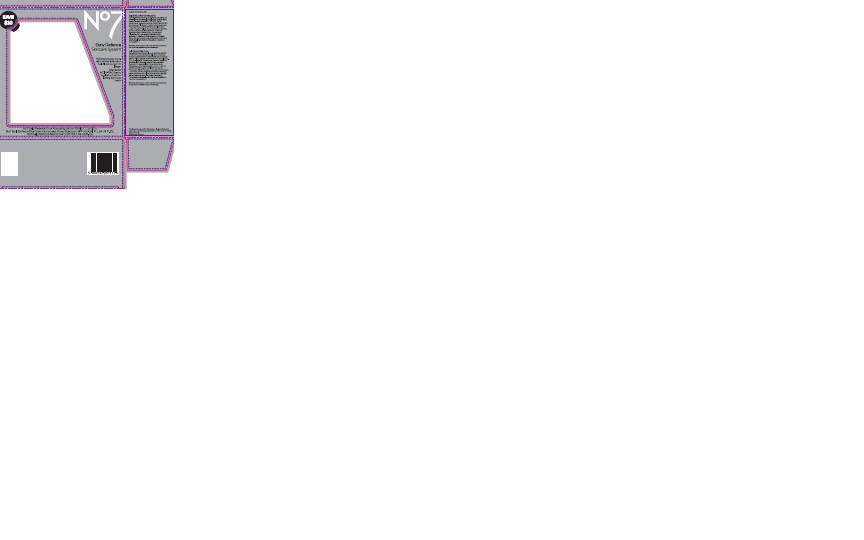 DRUG LABEL: No7 Early Defence Day Cream
NDC: 11489-126 | Form: CREAM
Manufacturer: BCM Ltd
Category: otc | Type: HUMAN OTC DRUG LABEL
Date: 20170808

ACTIVE INGREDIENTS: AVOBENZONE 1.5 g/1 g; OCTOCRYLENE 3.75 g/1 g; OCTISALATE 2.5 g/1 g
INACTIVE INGREDIENTS: WATER; GLYCERIN; ALUMINUM STARCH OCTENYLSUCCINATE; CETEARYL GLUCOSIDE; DIMETHICONE; TRIBEHENIN; AMMONIUM ACRYLOYLDIMETHYLTAURATE/VP COPOLYMER; PHENOXYETHANOL; SHEA BUTTER; POTASSIUM CETYL PHOSPHATE; BUTYLENE GLYCOL; DIMETHICONOL (100000 CST); PROPYLENE GLYCOL; METHYLPARABEN; ETHYLPARABEN; XANTHAN GUM; PANAX GINSENG ROOT OIL; VITAMIN A PALMITATE; ASCORBYL GLUCOSIDE; EDETATE SODIUM; TERT-BUTYL ALCOHOL; DIMETHYLMETHOXY CHROMANOL; POLYSORBATE 20; MEDICAGO SATIVA LEAF; POTASSIUM HYDROXIDE; CARBOMER 940; MORUS ALBA LEAF; ISOPROPYL MYRISTATE; SODIUM BENZOATE; ETHYLHEXYLGLYCERIN; TOCOPHEROL; PALMITOYL TRIPEPTIDE-1; PALMITOYL TETRAPEPTIDE-7

No7 Early Defence Day Cream Sunscreen Broad Spectrum SPF 30

Carton Active Ingredients Section

Active ingredients

Avobenzone 3%

Octisalate 5%

Octocrylene 7.5%

Uses

Uses - helps prevent sunburn

Warnings

For external use only

Do not use on damaged or broken skin

When using this product keep out of eyes. Rinse with water to remove.

Ask a doctor

Stop use and ask a doctor if rash occurs

Keep out of reach of children

If swallowed, get medical help or contact a Poison Control Center right away

Directions

Apply liberally 15 minutes before sun exposure

reapply at least every 2 hours

use a water resistant sunscreen if swimming or sweating

children under 6 months of age: Ask a doctor

Sun Protection Measures. Spending time in the sun increases your risk of skin cancer and early skin aging.

To decrease this risk, regularly use a sunscreen with a Broad Spectrum SPF value of 15 or higher and other sun protection measures including:

Limit time in the sun, especially from 10 a.m - 2 p.m.

wear long-sleeved shirts,pants,hats and sunglasses.

Storage

Other information

Protect the product in this container from excessive heat and direct sun

Avoid contact with fabrics

Inactive ingredients

Aqua(Water), Glycerin, C12-15 alkyl benzoate,Tribehenin, Alcohol denat, Dimethicone, Aluminum starch octenylsuccinate, Cetearyl glucoside, Butyrospermum parkii(Shea)butter, Ammonium acryloydimethyltaurate/VP copolymer, Phenoxyethanol, Potassium cetyl phosphate, Methylparaben, Parfum(Fragrance), Butylene glycol, Dimethiconol, Propylene glycol, Xanthan gum, Tocopheryl acetate, Ascorbyl glucoside, Ethylparaben, Retinyl palmitate, Hydrolyzed rice protein, Tetrasodium EDTA, T-butyl alcohol, Panax ginseng root extract, Dimethylmethoxy chromanol, Medicago sativa(Alfalfa) extract, Carbomer, Potassium hydroxide, Polysorbate 20, Morus alba leaf extract, Silica, Isopropyl myristate, Sodium benzoate, Tocopherol, Ethylhexylglycerin, Palmitoyl tripeptide-1, Palmitoyl tetrapeptide-7

Description

No7 Early Defence Skincare System

Protects and boosts young skin's natural defences to help it look younger for longer. With GLOW ACTIVATING Serum, for glowing, healthier looking skin in just 1 week.

No7 Early Defence Glow Activating Serum 30ml e 1 US Fl.Oz

No7 Early Defence Day Cream Sunscreen Broad Spectrum SPF 30 50ml e 1.69 US Fl.Oz.

No7 Early Defence Night Cream 50ml e 1.69 US Fl.Oz.

Description

Our best defence for young skin

When life is fast take control of your skin with No7's Early Defence Skincare, with super light formulations that work to keep young skin looking younger for longer.

This daily skincare system includes our No7 Early Defence Day and Night Creams, which work to slow down the effects that everyday life can have on young skin; as well as our Early Defence GLOW ACTIVATING Serum for glowing,healthier looking skin in just 1 week.

Enriched with our unique Double Defence technology - a powerful blend of antioxidants - the regime works to help protect your skin from every day environmental stress; while a combination of Lipopeptides with Vitamin A in our Day and Night Creams- and Matrixyl 3000 Plus TM in our serum - helps to reduce the appearance of those first fine lines.

Formulated by No7, leaders in age-defying skincare.

SERUM

Glowing, healthier looking skin in 1 week.

Your busy lifestyle, the sun & pollution all put stresses on your skin, dulling its natural radiance and even causing breakouts. Our formulation works to boost your skin's natural renewal process, helping clear and refine pores and get your skin glowing again. Day by day our unique Double Defence technology supports your skin's natural defences, reduces your skins's reactivity to stresses, and protects from everyday pollution. Powered by Matrixyl 3000 Plus TM to reduce the appearance of those first fine lines. After just 1 week skin appears more radiant and looks healthier and clearer, withe less visible pores.

DAY CREAM

This super-light and non pore-blocking day cream is formulated with the protective power of Sunscreen Broad Spectrum SPF 30 to help give your skin protection from the No 1 cause of visible skin ageing. Double Defence technology protects skin and boosts natural defences against environmental stress. Upon first application skin feels softer and looks more radiant. In just 2 weeks the appearance of pores is visibly reduced.

NIGHT CREAM

This super-light and non pore-blocking night cream works while you sleep to help skin recover from the day.

with Double Defence technology to give young skin effective night time protection against the damaging effects of free radicals generated from the sun and environmental stress during the day.

For Best Results: After cleansing, smooth No7 Early Defence Glow Activating Serum on to your face and neck. In the morning, follow with No7 Early Defence Day Cream. At night, follow with No7 Early Defence Night Cream.

PATIENT COUNSELING INFORMATION

The Boots Company PLC Nottingham England NG2 3AA

Dist. in the USA by Boots Retail USA Inc. New York NY 10005

Made in the UK

www.boots.com/no7